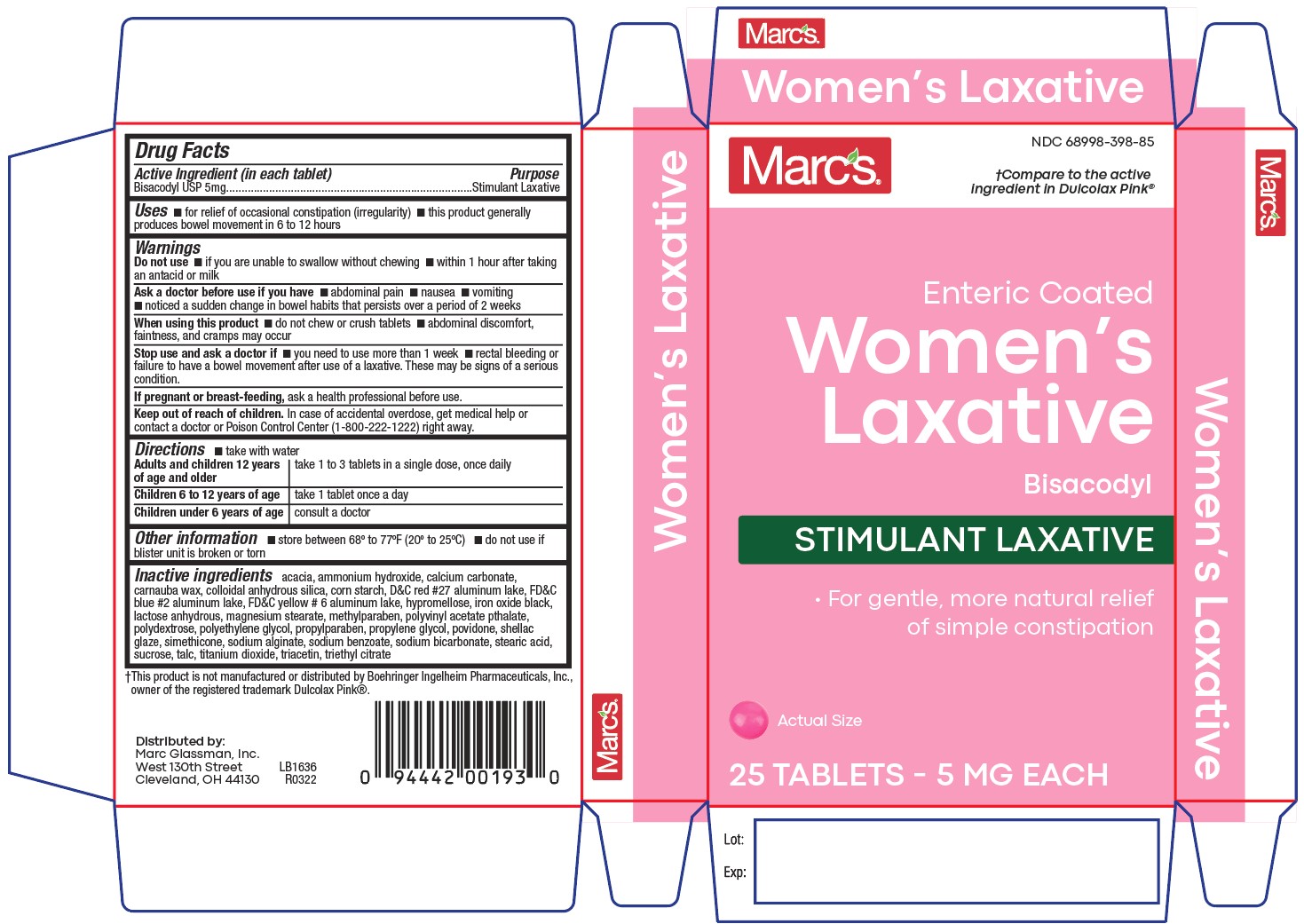 DRUG LABEL: Womens Laxative
NDC: 68998-398 | Form: TABLET, DELAYED RELEASE
Manufacturer: Marc Glassman, Inc.
Category: otc | Type: HUMAN OTC DRUG LABEL
Date: 20190917

ACTIVE INGREDIENTS: BISACODYL 5 mg/1 1
INACTIVE INGREDIENTS: ACACIA; MAGNESIUM STEARATE; POLYETHYLENE GLYCOL 400; POVIDONE; SHELLAC; STEARIC ACID; TALC; TITANIUM DIOXIDE; TRIACETIN; CALCIUM CARBONATE; CARNAUBA WAX; STARCH, CORN; D&C RED NO. 27; FD&C BLUE NO. 2--ALUMINUM LAKE; FD&C YELLOW NO. 6; HYPROMELLOSES; METHYLPARABEN; Polyvinyl Acetate Phthalate; POLYDEXTROSE; PROPYLENE GLYCOL; SODIUM ALGINATE; SODIUM BENZOATE; SODIUM BICARBONATE; SUCROSE; TRIETHYL CITRATE

Womens Laxative

Active ingredient

Bisacodyl USP 5mg

Purpose

Stimulant Laxative

Uses

- for relief of occasional constipation and irregularity
- this product usually causes bowel movements in 6 to 12 hours

Warnings

Do not use

- if you cannot swallow without chewing
- within 1 hour after taking antacid or milk

Ask a doctor before use if you have

- abdominal pain
- nausea
- vomiting
- notice a sudden change in bowel habits that persists over a period of 2 weeks

When using this product

- do not chew or crush tablets
- abdominal discomfort, faintness, and cramps may occur

Stop use and ask a doctor if

- you need to use more than 1 week
- rectal bleeding or failure to have a bowel movement after use of a laxative.

These may be signs of a serious condition.

Pregnancy/Breastfeeding

ask a health professional before use.

Keep out of reach of children

In case of accidental overdose, get medical help or contact a doctor or Poison Control Center (1-800-222-1222) right away.

Directions

- take with water

Adults and children 12 years of age and older: take 1 to 3 tablets in a single dose, once daily

Children 6 to 12 years of age: take 1 tablet once daily

Children under 6 years of age: consult a doctor

Other information

- store between 68º to 77ºF (20º to 25ºC)
- do not use if blister unit is broken or torn

Inactive ingredients

acacia, ammonium hydroxide, calcium carbonate, carnauba wax, colloidal anhydrous silica, corn starch, D&C red #27 aluminum lake, FD&C blue #2 aluminum lake, FD&C yellow # 6 aluminum lake, hypromellose, iron oxide black, lactose anhydrous, magnesium stearate, methylparaben, polyvinyl acetate pthalate, polydextrose, polyethylene glycol, propylparaben, propylene glycol, povidone, shellac glaze, simethicone, sodium alginate, sodium benzoate, sodium bicarbonate, stearic acid, sucrose, talc, titanium dioxide, triacetin, triethyl citrate

Principal Display Panel

Women's Laxative